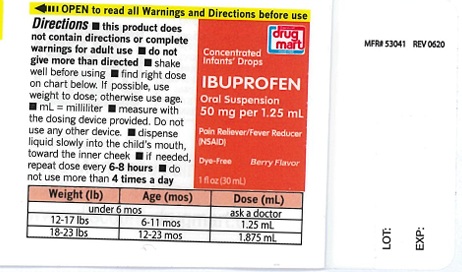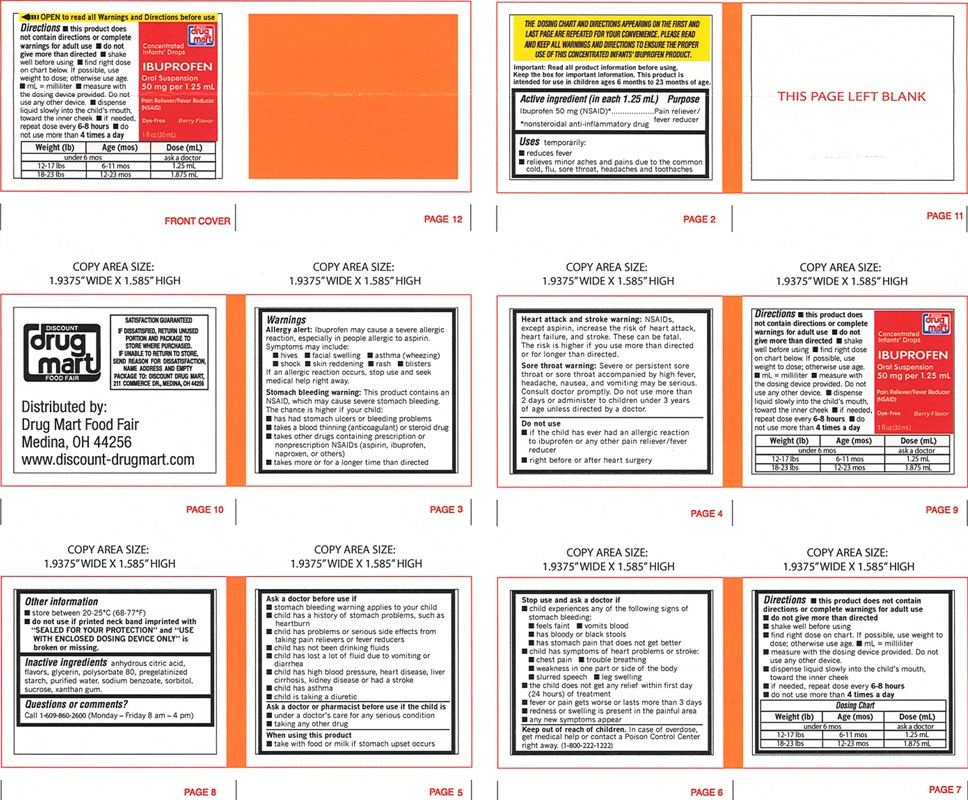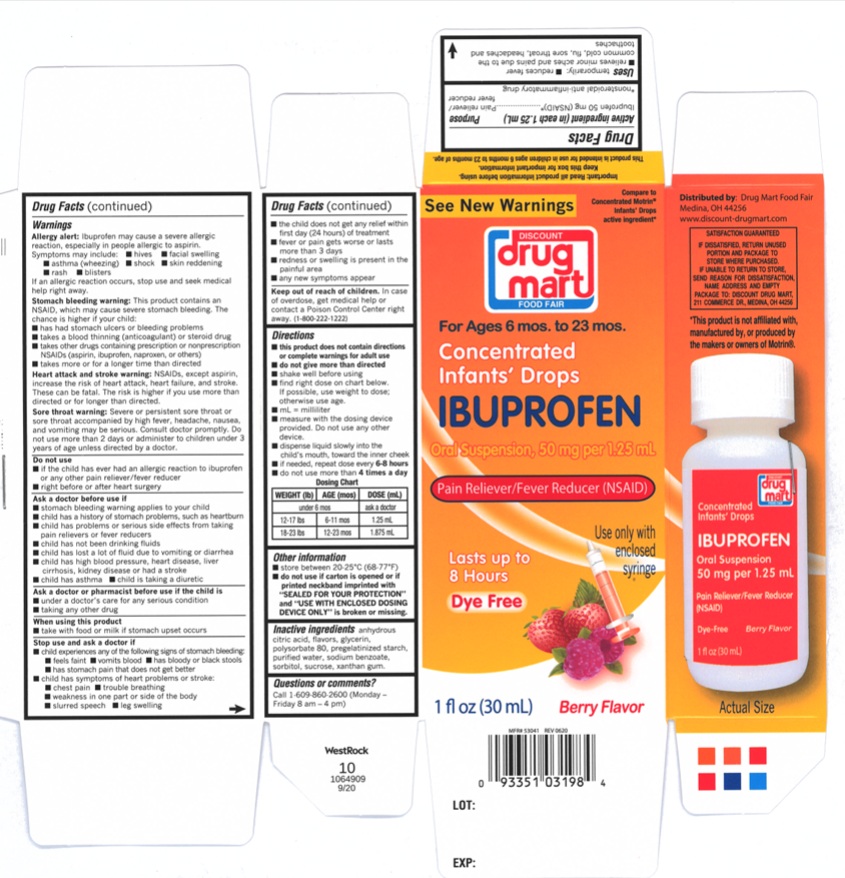 DRUG LABEL: Ibuprofen infants Drops
NDC: 53943-637 | Form: SUSPENSION/ DROPS
Manufacturer: Discount Drug Mart, Inc
Category: otc | Type: Human OTC Drug Label
Date: 20250224

ACTIVE INGREDIENTS: IBUPROFEN 50 mg/1.25 mL
INACTIVE INGREDIENTS: ANHYDROUS CITRIC ACID; GLYCERIN; POLYSORBATE 80; STARCH, CORN; WATER; SODIUM BENZOATE; SUCROSE; XANTHAN GUM; SORBITOL

Ibuprofen Infants Drops

ACTIVE INGREDIENT (in each 1.25 mL)

Ibuprofen 50 mg (NSAID)*
*nonsteroidal anti-inflammatory drug

PURPOSE

Pain reliever/fever reducer

USE(S)

temporarily:

- reduces fever
- relieves minor aches and pains due to the common cold, flu, sore throat, headaches and toothaches

WARNINGS

Allergy alert: Ibuprofen may cause a severe allergic reaction, especially in people allergic to aspirin. Symptoms may include:

- hives
- facial swelling
- asthma (wheezing)
- shock
- skin reddening
- rash
- blisters

If an allergic reaction occurs, stop use and seek medical help right away.
Stomach bleeding warning: This product contains an NSAID, which may cause severe stomach bleeding. The chance is higher if you child:

- has had stomach ulcers or bleeding problems
- takes a blood thinning (anticoagulant) or steroid drug
- takes other drugs containing prescription or nonprescription NSAIDs (aspirin, ibuprofen, naproxen, or others)
- takes more or for a longer time than directed

Heart attack and stroke warning: NSAIDs, except aspirin, increase the risk of heart attack, heart failure and stroke. These can be fatal. The risk is higher if you use more than directed or for longer than directed.
Sore throat warning: Severe or persistent sore throat or sore throat accompanied by high fever, headache, nausea, and vomiting may be serious. Consult doctor promptly. Do not use more than 2 days or administer to children under 3 years of age unless directed by doctor.

DO NOT USE

- if the child has ever had an allergic reaction to ibuprofen or any other pain reliever/fever reducer
- right before or after heart surgery

ASK A DOCTOR BEFORE USE IF

- stomach bleeding warning applies to your child
- child has a history of stomach problems, such as heartburn
- child has problems or serious side effects from taking pain relievers or fever reducers
- child has not been drinking fluids
- child has lost a lot of fluid due to vomiting or diarrhea
- child has high blood pressure, heart disease, liver cirrhosis, kidney disease or had a stroke
- child has asthma
- child is taking a diuretic

ASK A DOCTOR OR PHARMACIST BEFORE USE IF THE CHILD IS

- under a doctor's care for any serious condition
- taking any other drug

WHEN USING THIS PRODUCT

- take with food or milk if stomach upset occurs

STOP USE AND ASK DOCTOR IF

- child experiences any of the following signs of stomach bleeding:
- feels faint
- vomits blood
- has bloody or black stools
- has stomach pain that does not get better
- child has symptoms of heart problems or stroke:
- chest pain
- trouble breathing
- weakness in one part or side of the body
- slurred speech
- leg swelling
- the child does not get any relief within first day (24 hours) of treatment
- fever or pain gets worse or lasts more than 3 days
- redness or swelling is present in the painful area
- any new symptoms appear

KEEP OUT OF REACH OF CHILDREN

In case of overdose, get medical help or contact a Poison Control Center right away. (1-800-222-1222)

DIRECTIONS

- this product does not contain directions or complete warnings for adult use
- do not give more than directed
- shake well before using
- find right dose on chart below. If possible, use weight to dose; otherwise use age.
- mL=milliliter
- measure with dosing device provided. Do not use any other dosing device.
- dispense liquid slowly into the child's mouth, toward the inner cheek
- if needed, repeat dose every 6-8 hours
- do not use more than 4 times a day

Dosing Chart

WEIGHT (lb) | AGE (mos) | DOSE (mL)
under 6 mos |  | ask a doctor
12-17 lbs | 6-11 mos | 1.25 mL
18-23 lbs | 12-23 years | 1.875 mL

OTHER INFORMATION

- store between 20-25oC (68-77oF)
- do not use if carton is opened or if printed neckband is imprinted with "SEALED FOR YOUR PROTECTION" and "USE WITH ENCLOSED DOSING DEVICE ONLY" is broken or missing.

INACTIVE INGREDIENTS

anhydrous citric acid, flavors, glycerin, polysorbate 80, pregelatinized starch, purified water, sodium benzoate, sorbitol, sucrose, xanthan gum

QUESTIONS OR COMMENTS?

call 1-609-860-2600 (Monday - Friday 8:00 am - 4:30 pm EST)

PRINCIPAL DISPLAY PANEL

Compare to Concentrated Motrin® Infants' Drops active ingredient*

See New Warnings

NDC 53943-637-09

Discount drug mart

FOOD FAIR

For Ages 6 mos. to 23 mos.
Concentrated Infants' Drops
IBUPROFEN

Oral Suspension, 50 mg per 1.25 mL
Pain Reliever /Fever Reducer (NSAID)

Lasts Up to

8 Hours

Dye-Free

Use Only With Enclosed Syringe

1 fl oz (30 mL) Berry Flavor